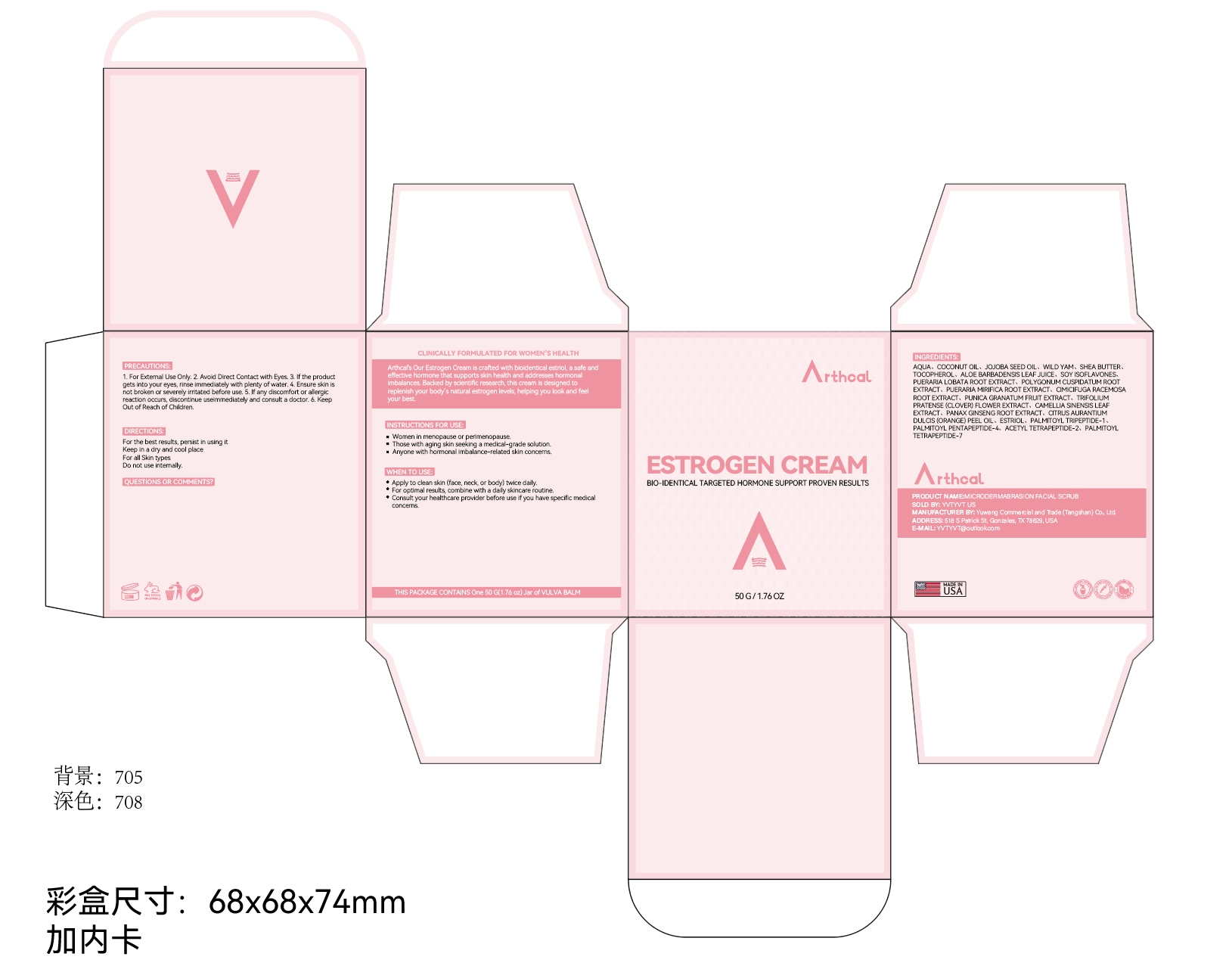 DRUG LABEL: Arthcal Estriol Face Cream for Women
NDC: 85212-0016 | Form: CREAM
Manufacturer: Beijing JUNGE Technology Co., Ltd.
Category: otc | Type: HUMAN OTC DRUG LABEL
Date: 20250228

ACTIVE INGREDIENTS: TOCOPHEROL 1 g/100 g; BUTYROSPERMUM PARKII (SHEA) BUTTER 2 g/100 g; ESTRIOL 0.2 g/100 g
INACTIVE INGREDIENTS: CIMICIFUGA RACEMOSA ROOT 0.1 g/100 g; PUNICA GRANATUM WHOLE 0.1 g/100 g; AQUA 74.21 g/100 g; BUTYLENE GLYCOL 5 g/100 g; GLYCERIN 5 g/100 g; CETEARYL ALCOHOL 1 g/100 g; PUERARIA MIRIFICA ROOT 0.5 g/100 g; SIMMONDSIA CHINENSIS (JOJOBA) SEED OIL 2 g/100 g; PANAX GINSENG ROOT 0.1 g/100 g; TRIFOLIUM PRATENSE (CLOVER) FLOWER 0.1 g/100 g; CAMELLIA SINENSIS LEAF OIL 0.1 g/100 g; ARGININE 0.015 g/100 g; CAPRYLYL GLYCOL 0.015 g/100 g; CITRUS AURANTIUM DULCIS (ORANGE) PEEL OIL 0.015 g/100 g; HYALURONIC ACID 0.015 g/100 g; ALOE BARBADENSIS LEAF JUICE 0.5 g/100 g; SOY ISOFLAVONES 0.5 g/100 g; CARBOMER 0.015 g/100 g; 1,2-HEXANEDIOL 0.015 g/100 g; COCOS NUCIFERA (COCONUT) OIL 5 g/100 g; POLYGONUM CUSPIDATUM ROOT 0.5 g/100 g; SQUALANE 2 g/100 g

DOSAGE AND ADMINISTRATION

50G/1.76OZ

INDICATIONS AND USAGE

Apply to clean skin (face, neck, or body) twice daily.
For optimal results, combine with a daily skincare routine.
Consult your healthcare provider before use if you have specific medical concerns.

PRECAUTIONS

1. For Extemal Use Only. 2. Avoid Direct Contact with Eyes. 3. If the product
gets into your eyes, rinse immediately with plenty of water. 4. Ensure skin is
not broken or severely irritated before use. 5. If any discomfort dor alergic
reaction occurs, discontinue useimmediately and consult a doctor. 6. Keep
Out of Reach of Children.

INSTRUCTIONS FOR USE

Women in menopause or perimenopause.
Those with aging skin seeking a medical-grade solution.
Anyone with hormonal imbalance-related skin concerns.

ACTIVE INGREDIENT

BUTYROSPERMUM PARKII (SHEA BUTTER)
TOCOPHEROL
Estriol

INACTIVE INGREDIENT

AQUA
BUTYLENE GLYCOL
GLYCERIN
COCOS NUCIFERA (COCONUT) OIL
SIMMONDSIA CHINENSIS (JOJOBA) SEED OIL
SQUALANE
CETEARYL ALCOHOL
ALOE BARBADENSIS LEAF JUICE
SOY ISOFLAVONES
POLYGONUM CUSPIDATUM ROOT EXTRACT
PUERARIA MIRIFICA ROOT EXTRACT
CIMICIFUGA RACEMOSA ROOT EXTRACT
PUNICA GRANATUM FRUIT EXTRACT
TRIFOLIUM PRATENSE (CLOVER) FLOWER EXTRACT
CAMELLIA SINENSIS LEAF EXTRACT
PANAX GINSENG ROOT EXTRACT
CITRUS AURANTIUM DULCIS (ORANGE) PEEL OIL
HYALURONIC ACID
CARBOMER
ARGININE
1,2-HEXANEDIOL
CAPRYLYL GLYCOL

PURPOSE

Reduce Hot Flashes
Menopause Relief
Menstrual Cycle Support
Hormone Balance

Keep out of reach of children. If swallowed, get medical help or contact a Poison Control Center right away

WARNINGS

For external use only. Keep out of reach of children.Avoid contact with eyes.